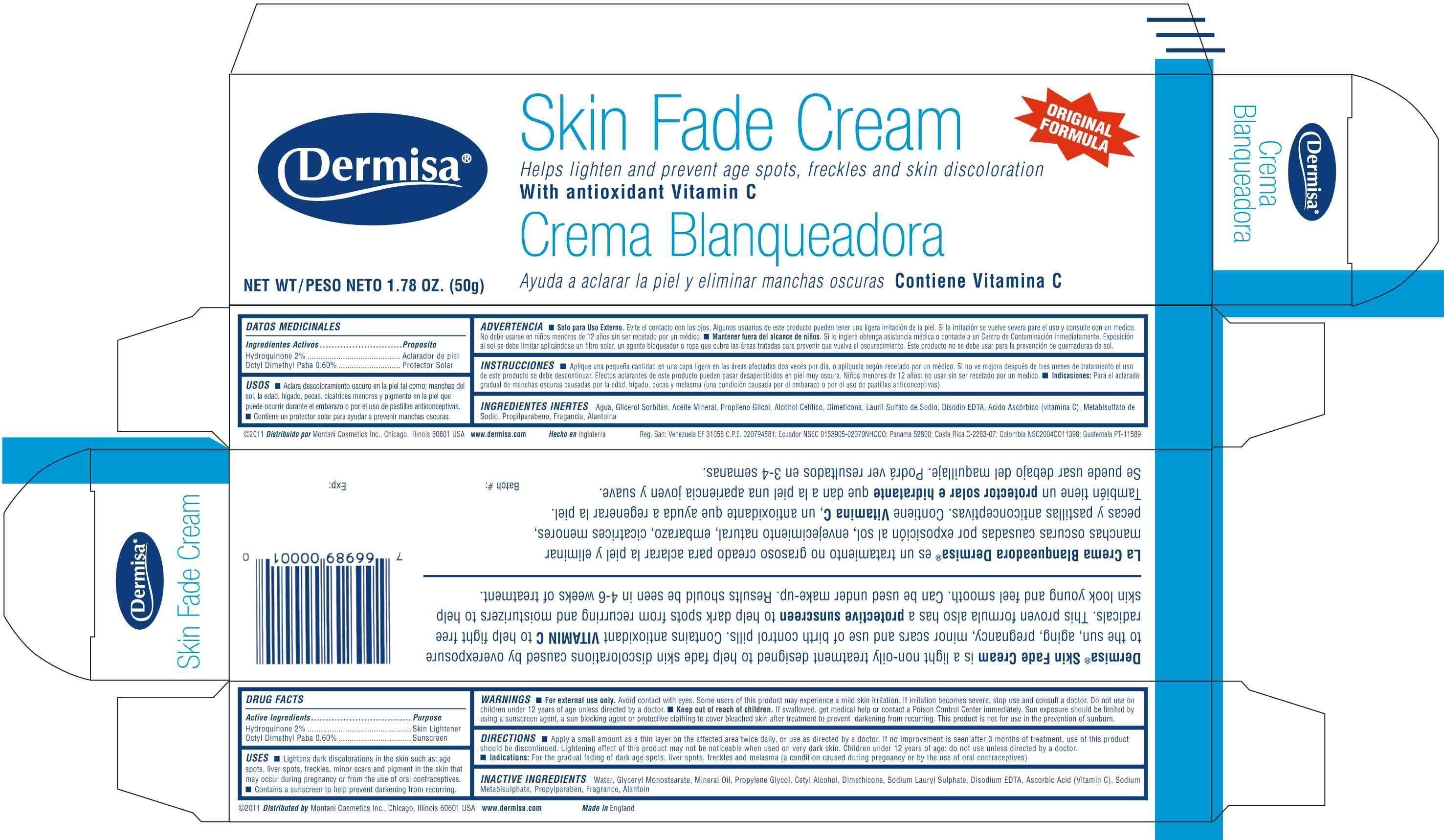 DRUG LABEL: Dermisa
NDC: 68343-001 | Form: CREAM
Manufacturer: Montani Cosmetics Inc
Category: otc | Type: HUMAN OTC DRUG LABEL
Date: 20180719

ACTIVE INGREDIENTS: HYDROQUINONE 2 g/100 g; PADIMATE O 0.6 g/100 g
INACTIVE INGREDIENTS: WATER; MINERAL OIL; GLYCERYL MONOSTEARATE; PROPYLENE GLYCOL; CETYL ALCOHOL; DIMETHICONE; SODIUM LAURYL SULFATE; EDETATE DISODIUM; ASCORBIC ACID; SODIUM METABISULFITE; PROPYLPARABEN; ALLANTOIN

Drug Facts

Active Ingredient

Hydroquinone USP 2%
Octyl Dimethyl Paba 0.60%

Purpose

Skin Lightener
Sunscreen

Use

- Lightens dark discolorations in the skin such as age spots, liver spots, freckles, minor scars and pigment in skin that may occur during pregnancy or from the use of oral contraceptives.
- Contains a sunscreen to help prevent darkening from reoccurring.

Warnings

- For external use only. Avoid contact with eyes. Some users of this product may experience a mild skin irritation. If irritation becomes severe, stop use and consult a doctor. Do not use on children under 12 years of age unless directed by a doctor. Sun exposure should be limited by using a sunscreen agent, a sunblocking agent or protective clothing to cover bleached skin after treatment to prevent darkening from recurring. This product is not for the use in the prevention of sunburn

Keep out of reach of children

- If swallowed, get medical help or contact a Poison Control Center immediately.

Directions

- Apply a small amount as a thin layer to the affected areas twice daily or as directed by a doctor. If no improvement is seen after 3 months of treatment, use of this product should be discontinued.Lightening effect of this product may not be noticeable when used on very dark skin. Children under 12 years of age: do not use unless directed by a doctor.
- Indications: For the gradual fading of dark age spots, liver spots, freckles and melasma (a condition caused during pregnancy or by the use of oral contraceptives)

Inactive ingredients

Water, Glyceryl Monostearate, Mineral Oil, Propylene Glycol, Cetyl Alcohol, Dimethicone, Sodium Lauryl Sulphate, Disodium EDTA, Ascorbic Acid (Vitamin C), Sodium Metabisulphite, Propylparaben, Fragrance, Allantoin